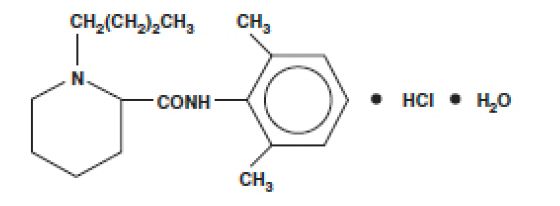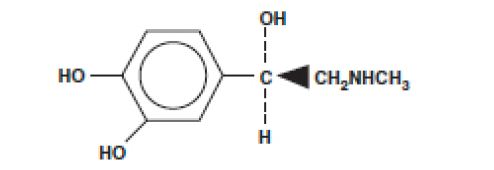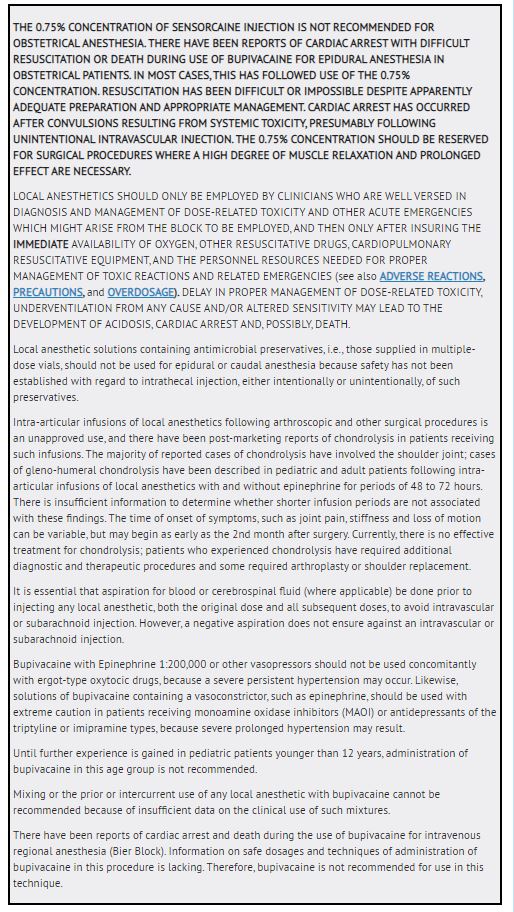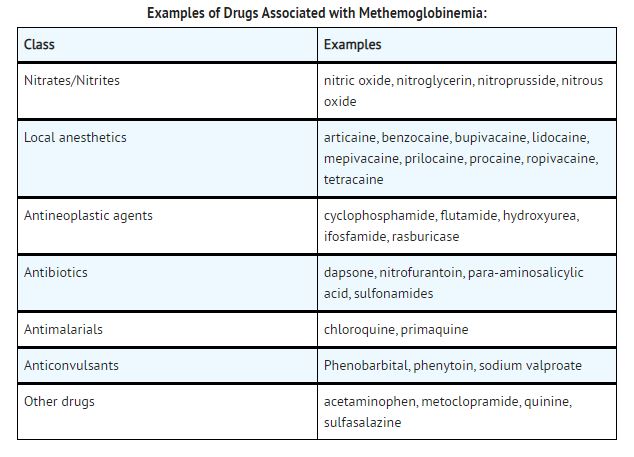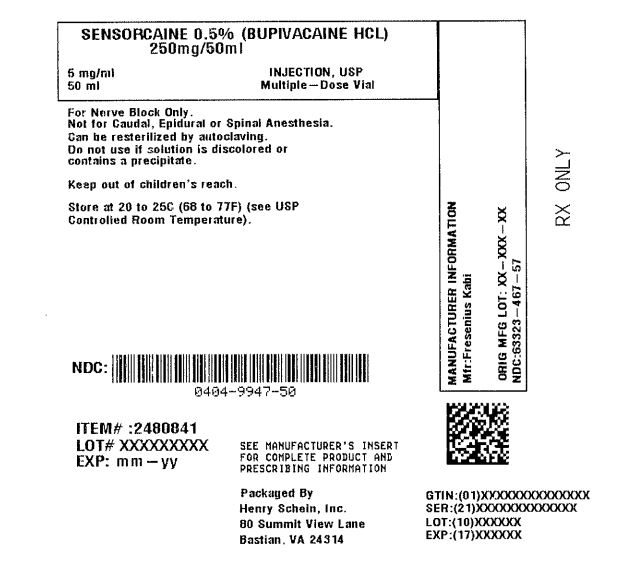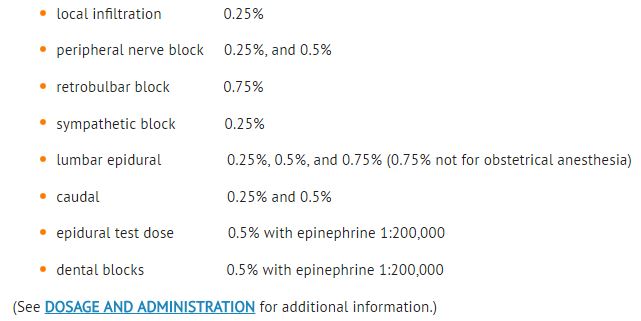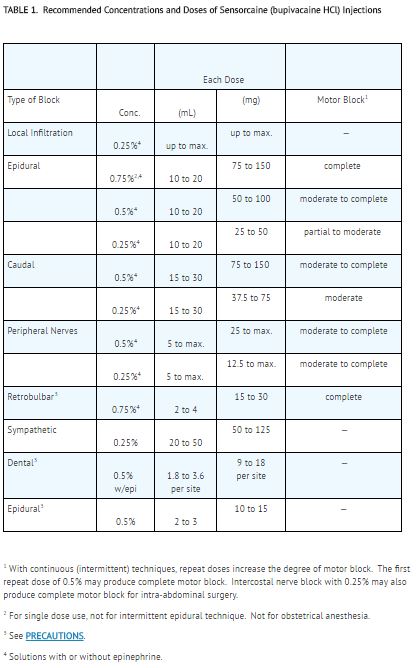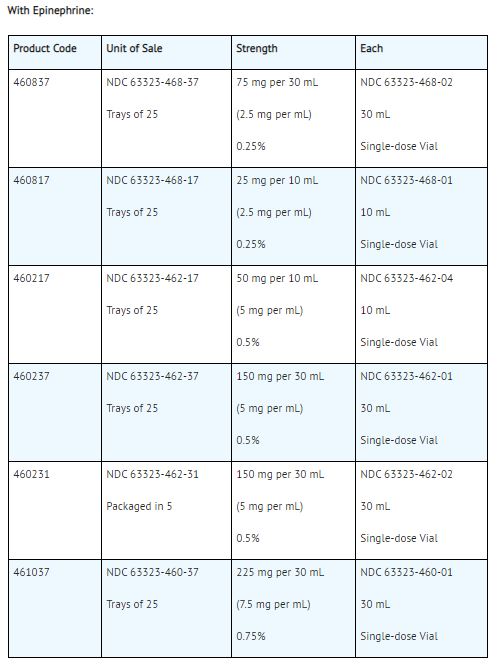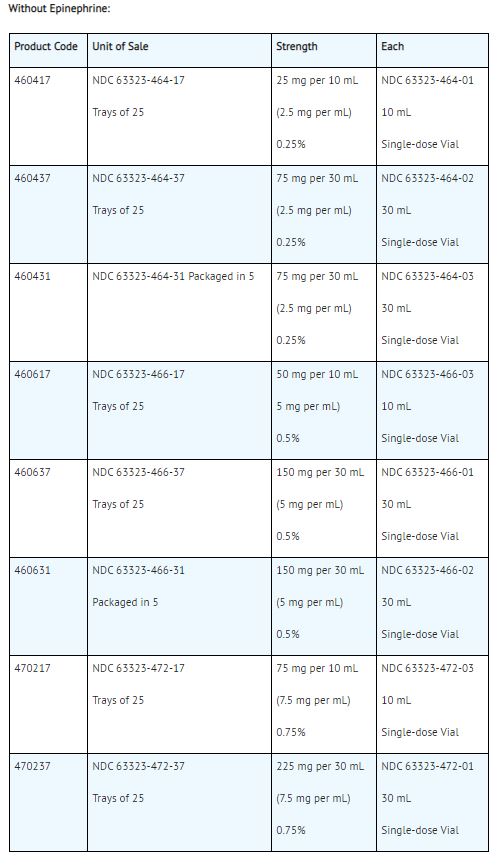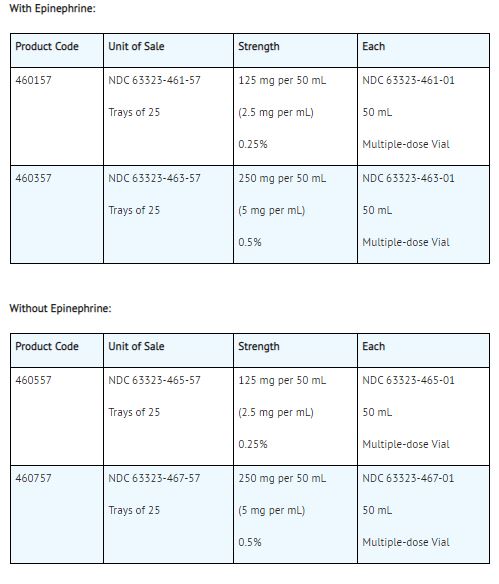 DRUG LABEL: Sensorcaine
NDC: 0404-9947 | Form: INJECTION, SOLUTION
Manufacturer: Henry Schein, Inc.
Category: prescription | Type: HUMAN PRESCRIPTION DRUG LABEL
Date: 20251107

ACTIVE INGREDIENTS: BUPIVACAINE HYDROCHLORIDE 5 mg/1 mL
INACTIVE INGREDIENTS: SODIUM CHLORIDE 8 mg/1 mL; METHYLPARABEN 1 mg/1 mL; SODIUM HYDROXIDE; HYDROCHLORIC ACID

451106H /Revised: March 2019Sensorcaine
Sensorcaine -MPF
Rx only Sensorcaine (bupivacaine HCl Injection, USP)
Sensorcaine -MPF (bupivacaine HCl Injection, USP)
Sensorcaine with Epinephrine (bupivacaine HCl and epinephrine injection, USP) 1:200,000 (as bitartrate)
Sensorcaine -MPF with Epinephrine (bupivacaine HCl and epinephrine Injection, USP) 1:200,000 (as bitartrate)

DESCRIPTION

Sensorcaine ® (bupivacaine HCl) injections are sterile isotonic solutions that contain a local anesthetic agent with and without epinephrine (as bitartrate) 1:200,000 and are administered parenterally by injection. See INDICATIONS AND USAGE for specific uses. Solutions of bupivacaine HCl may be autoclaved if they do not contain epinephrine.

Sensorcaine injections contain bupivacaine HCl which is chemically designated as 2-piperidinecarboxamide, 1-butyl-N-(2,6-dimethylphenyl)-, monohydrochloride, monohydrate and has the following structure:

Epinephrine is (-)-3, 4-Dihydroxy-a [(methylamino)methyl] benzyl alcohol. It has the following structural formula:

The pKa of bupivacaine (8.1) is similar to that of lidocaine (7.86). However, bupivacaine possesses a greater degree of lipid solubility and is protein bound to a greater extent than lidocaine.

Bupivacaine is related chemically and pharmacologically to the aminoacyl local anesthetics. It is a homologue of mepivacaine and is chemically related to lidocaine. All three of these anesthetics contain an amide linkage between the aromatic nucleus and the amino, or piperidine group. They differ in this respect from the procaine-type local anesthetics, which have an ester linkage.

Dosage forms listed as Sensorcaine-MPF indicates single dose solutions that are Methyl Paraben Free (MPF).

Sensorcaine-MPF is a sterile isotonic solution containing sodium chloride. Sensorcaine in multiple dose vials, each mL also contains 1 mg methylparaben as antiseptic preservative. The pH of these solutions is adjusted to between 4.0 and 6.5 with sodium hydroxide and/or hydrochloric acid.

Sensorcaine-MPF with Epinephrine 1:200,000 (as bitartrate) is a sterile isotonic solution containing sodium chloride. Each mL contains bupivacaine hydrochloride and 0.005 mg epinephrine, with 0.5 mg sodium metabisulfite as an antioxidant and 0.2 mg citric acid (anhydrous) as stabilizer. Sensorcaine with Epinephrine 1:200,000 (as bitartrate) in multiple dose vials, each mL also contains 1 mg methylparaben as antiseptic preservative. The pH of these solutions is adjusted to between 3.3 to 5.5 with sodium hydroxide and/or hydrochloric acid. Filled under nitrogen.

Note: The user should have an appreciation and awareness of the formulations and their intended uses (see DOSAGE AND ADMINISTRATION).

CLINICAL PHARMACOLOGY

Local anesthetics block the generation and the conduction of nerve impulses, presumably by increasing the threshold for electrical excitation in the nerve, by slowing the propagation of the nerve impulse, and by reducing the rate of rise of the action potential. In general, the progression of anesthesia is related to the diameter, myelination, and conduction velocity of affected nerve fibers. Clinically, the order of loss of nerve function is as follows: (1) pain, (2) temperature, (3) touch, (4) proprioception, and (5) skeletal muscle tone.

Systemic absorption of local anesthetics produces effects on the cardiovascular and central nervous systems (CNS). At blood concentrations achieved with normal therapeutic doses, changes in cardiac conduction, excitability, refractoriness, contractility, and peripheral vascular resistance are minimal. However, toxic blood concentrations depress cardiac conduction and excitability, which may lead to atrioventricular block, ventricular arrhythmias and cardiac arrest, sometimes resulting in fatalities. In addition, myocardial contractility is depressed and peripheral vasodilation occurs, leading to decreased cardiac output and arterial blood pressure. Recent clinical reports and animal research suggest that these cardiovascular changes are more likely to occur after unintended intravascular injection of bupivacaine. Therefore, incremental dosing is necessary.

Following systemic absorption, local anesthetics can produce central nervous system stimulation, depression, or both. Apparent central stimulation is manifested as restlessness, tremors and shivering progressing to convulsions, followed by depression and coma progressing ultimately to respiratory arrest. However, the local anesthetics have a primary depressant effect on the medulla and on higher centers. The depressed stage may occur without a prior excited state.

Pharmacokinetics

The rate of systemic absorption of local anesthetics is dependent upon the total dose and concentration of drug administered, the route of administration, the vascularity of the administration site, and the presence or absence of epinephrine in the anesthetic solution. A dilute concentration of epinephrine (1:200,000 or 5 mcg/mL) usually reduces the rate of absorption and peak plasma concentration of bupivacaine, permitting the use of moderately larger total doses and sometimes prolonging the duration of action.

The onset of action with bupivacaine is rapid and anesthesia is long lasting. The duration of anesthesia is significantly longer with bupivacaine than with any other commonly used local anesthetic. It has also been noted that there is a period of analgesia that persists after the return of sensation, during which time the need for strong analgesics is reduced.

The onset of action following dental injections is usually 2 to 10 minutes and anesthesia may last two or three times longer than lidocaine and mepivacaine for dental use, in many patients up to 7 hours. The duration of anesthetic effect is prolonged by the addition of epinephrine 1:200,000.

Local anesthetics are bound to plasma proteins in varying degrees. Generally, the lower the plasma concentration of drug the higher the percentage of drug bound to plasma proteins.

Local anesthetics appear to cross the placenta by passive diffusion. The rate and degree of diffusion is governed by (1) the degree of plasma protein binding, (2) the degree of ionization, and (3) the degree of lipid solubility. Fetal/maternal ratios of local anesthetics appear to be inversely related to the degree of plasma protein binding, because only the free, unbound drug is available for placental transfer.

Bupivacaine with a high protein binding capacity (95%) has a low fetal/maternal ratio (0.2 to 0.4). The extent of placental transfer is also determined by the degree of ionization and lipid solubility of the drug. Lipid soluble, nonionized drugs readily enter the fetal blood from the maternal circulation.

Depending upon the route of administration, local anesthetics are distributed to some extent to all body tissues, with high concentrations found in highly perfused organs such as the liver, lungs, heart, and brain.

Pharmacokinetic studies on the plasma profile of bupivacaine after direct intravenous injection suggest a three-compartment open model. The first compartment is represented by the rapid intravascular distribution of the drug. The second compartment represents the equilibration of the drug throughout the highly perfused organs such as the brain, myocardium, lungs, kidneys, and liver. The third compartment represents an equilibration of the drug with poorly perfused tissues, such as muscle and fat. The elimination of drug from tissue distribution depends largely upon the ability of binding sites in the circulation to carry it to the liver where it is metabolized.

After injection of Sensorcaine (bupivacaine HCl) for caudal, epidural, or peripheral nerve block in man, peak levels of bupivacaine in the blood are reached in 30 to 45 minutes, followed by a decline to insignificant levels during the next 3 to 6 hours.

Various pharmacokinetic parameters of the local anesthetics can be significantly altered by the presence of hepatic or renal disease, addition of epinephrine, factors affecting urinary pH, renal blood flow, the route of drug administration, and the age of the patient. The half-life of bupivacaine in adults is 2.7 hours and in neonates 8.1 hours.

In clinical studies, elderly patients reached the maximal spread of analgesia and maximal motor blockade more rapidly than younger patients. Elderly patients also exhibited higher peak plasma concentrations following administration of this product. The total plasma clearance was decreased in these patients.

Amide-type local anesthetics such as bupivacaine are metabolized primarily in the liver via conjugation with glucuronic acid. Patients with hepatic disease, especially those with severe hepatic disease, may be more susceptible to the potential toxicities of the amide-type local anesthetics. Pipecoloxylidine is the major metabolite of bupivacaine.

The kidney is the main excretory organ for most local anesthetics and their metabolites. Urinary excretion is affected by urinary perfusion and factors affecting urinary pH. Only 6% of bupivacaine is excreted unchanged in the urine.

When administered in recommended doses and concentrations, Sensorcaine (bupivacaine HCl) does not ordinarily produce irritation or tissue damage.

INDICATIONS & USAGE

Sensorcaine (bupivacaine HCl) is indicated for the production of local or regional anesthesia or analgesia for surgery, dental and oral surgery procedures, diagnostic and therapeutic procedures, and for obstetrical procedures. Only the 0.25% and 0.5% concentrations are indicated for obstetrical anesthesia (see WARNINGS).

Experience with nonobstetrical surgical procedures in pregnant patients is not sufficient to recommend use of the 0.75% concentration of bupivacaine HCl in these patients.

Sensorcaine is not recommended for intravenous regional anesthesia (Bier Block) (see WARNINGS). The routes of administration and indicated Sensorcaine concentrations are:

Standard textbooks should be consulted to determine the accepted procedures and techniques for the administration of Sensorcaine.

CONTRAINDICATIONS

Sensorcaine (bupivacaine HCl) is contraindicated in obstetrical paracervical block anesthesia. Its use in this technique has resulted in fetal bradycardia and death.

Sensorcaine is contraindicated in patients with a known hypersensitivity to it or to any local anesthetic agent of the amide-type or to other components of bupivacaine solutions.

WARNINGS

Methemoglobinemia:

Cases of methemoglobinemia have been reported in association with local anesthetic use. Although all patients are at risk for methemoglobinemia, patients with glucose-6-phosphate dehydrogenase deficiency, congenital or idiopathic methemoglobinemia, cardiac or pulmonary compromise, infants under 6 months of age, and concurrent exposure to oxidizing agents or their metabolites are more susceptible to developing clinical manifestations of the condition. If local anesthetics must be used in these patients, close monitoring for symptoms and signs of methemoglobinemia is recommended.Signs of methemoglobinemia may occur immediately or may be delayed some hours after exposure, and are characterized by a cyanotic skin discoloration and/or abnormal coloration of the blood. Methemoglobin levels may continue to rise; therefore, immediate treatment is required to avert more serious central nervous system and cardiovascular adverse effects, including seizures, coma, arrhythmias, and death. Discontinue Sensorcaine and any other oxidizing agents. Depending on the severity of the signs and symptoms, patients may respond to supportive care, i.e., oxygen therapy, hydration. A more severe clinical presentation may require treatment with methylene blue, exchange transfusion, or hyperbaric oxygen.Sensorcaine with epinephrine 1:200,000 contains sodium metabisulfite, a sulfite that may cause allergic- type reactions including anaphylactic symptoms and life-threatening or less severe asthmatic episodes in certain susceptible people. The overall prevalence of sulfite sensitivity in the general population is unknown and probably low. Sulfite sensitivity is seen more frequently in asthmatic than in nonasthmatic people. Sensorcaine and Sensorcaine - MPF without epinephrine single dose vials do not contain sodium metabisulfite.

PRECAUTIONS

General

The safety and effectiveness of local anesthetics depend on proper dosage, correct technique, adequate precautions, and readiness for emergencies. Resuscitative equipment, oxygen, and other resuscitative drugs should be available for immediate use (see WARNINGS, ADVERSE REACTIONS, and OVERDOSAGE). During major regional nerve blocks, the patient should have IV fluids running via an indwelling catheter to assure a functioning intravenous pathway. The lowest dosage of local anesthetic that results in effective anesthesia should be used to avoid high plasma levels and serious adverse effects. The rapid injection of a large volume of local anesthetic solution should be avoided and fractional (incremental) doses should be used when feasible.

Epidural Anesthesia

During epidural administration of Sensorcaine (bupivacaine HCl), 0.5% and 0.75% solutions should be administered in incremental doses of 3 mL to 5 mL with sufficient time between doses to detect toxic manifestations of unintentional intravascular or intrathecal injection. Injections should be made slowly, with frequent aspirations before and during the injection to avoid intravascular injection. Syringe aspirations should also be performed before and during each supplemental injection in continuous (intermittent) catheter techniques. An intravascular injection is still possible even if aspirations for blood are negative.

During the administration of epidural anesthesia, it is recommended that a test dose be administered initially and the effects monitored before the full dose is given. When using a “continuous” catheter technique, test doses should be given prior to both the original and all reinforcing doses, because plastic tubing in the epidural space can migrate into a blood vessel or through the dura. When clinical conditions permit, the test dose should contain epinephrine (10 mcg to 15 mcg has been suggested) to serve as a warning of unintended intravascular injection. If injected into a blood vessel, this amount of epinephrine is likely to produce a transient “epinephrine response” within 45 seconds, consisting of an increase in heart rate and/or systolic blood pressure, circumoral pallor, palpitations, and nervousness in the unsedated patient. The sedated patient may exhibit only a pulse rate increase of 20 or more beats per minute for 15 or more seconds. Therefore, following the test dose, the heart rate should be monitored for a heart rate increase. Patients on beta-blockers may not manifest changes in heart rate, but blood pressure monitoring can detect a transient rise in systolic blood pressure. The test dose should also contain 10 mg to 15 mg of Sensorcaine or an equivalent amount of another local anesthetic to detect an unintended intrathecal administration. This will be evidenced within a few minutes by signs of spinal block (e.g., decreased sensation of the buttocks, paresis of the legs, or, in the sedated patient, absent knee jerk). An intravascular or subarachnoid injection is still possible even if results of the test dose are negative. The test dose itself may produce a systemic toxic reaction, high spinal or epinephrine- induced cardiovascular effects.

Injection of repeated doses of local anesthetics may cause significant increases in plasma levels with each repeated dose due to slow accumulation of the drug or its metabolites, or to slow metabolic degradation. Tolerance to elevated blood levels varies with the status of the patient. Debilitated, elderly patients and acutely ill patients should be given reduced doses commensurate with their age and physical status. Local anesthetics should also be used with caution in patients with hypotension or heartblock.

Careful and constant monitoring of cardiovascular and respiratory (adequacy of ventilation) vital signs and the patient's state of consciousness should be performed after each local anesthetic injection. It should be kept in mind at such times that restlessness, anxiety, incoherent speech, lightheadedness, numbness and tingling of the mouth and lips, metallic taste, tinnitus, dizziness, blurred vision, tremors, twitching, depression, or drowsiness may be early warning signs of central nervous system toxicity.

Local anesthetic solutions containing a vasoconstrictor should be used cautiously and in carefully restricted quantities in areas of the body supplied by end arteries or having otherwise compromised blood supply such as digits, nose, external ear, or penis. Patients with hypertensive vascular disease may exhibit exaggerated vasoconstrictor response. Ischemic injury or necrosis may result.

Because amide-local anesthetics such as bupivacaine are metabolized by the liver, these drugs, especially repeat doses, should be used cautiously in patients with hepatic disease. Patients with severe hepatic disease, because of their inability to metabolize local anesthetics normally, are at a greater risk of developing toxic plasma concentrations. Local anesthetics should also be used with caution in patients with impaired cardiovascular function because they may be less able to compensate for functional changes associated with the prolongation of AV conduction produced by these drugs.

Serious dose-related cardiac arrhythmias may occur if preparations containing a vasoconstrictor such as epinephrine are employed in patients during or following the administration of potent inhalation anesthetics. In deciding whether to use these products concurrently in the same patient, the combined action of both agents upon the myocardium, the concentration and volume of vasoconstrictor used, and the time since injection, when applicable, should be taken into account.

Many drugs used during the conduct of anesthesia are considered potential triggering agents for familial malignant hyperthermia. Because it is not known whether amide-type local anesthetics may trigger this reaction and because the need for supplemental general anesthesia cannot be predicted in advance, it is suggested that a standard protocol for management should be available. Early unexplained signs of tachycardia, tachypnea, labile blood pressure, and metabolic acidosis may precede temperature elevation. Successful outcome is dependent on early diagnosis, prompt discontinuance of the suspect triggering agent(s) and prompt institution of treatment, including oxygen therapy, indicated supportive measures and dantrolene (consult dantrolene sodium intravenous package insert before using).

Use in Head and Neck Area

Small doses of local anesthetics injected into the head and neck area, including retrobulbar, dental and stellate ganglion blocks, may produce adverse reactions similar to systemic toxicity seen with unintentional intravascular injections of larger doses. The injection procedures require the utmost care. Confusion, convulsions, respiratory depression, and/or respiratory arrest, and cardiovascular stimulation or depression have been reported. These reactions may be due to intra-arterial injection of the local anesthetic with retrograde flow to the cerebral circulation. They may also be due to puncture of the dural sheath of the optic nerve during retrobulbar block with diffusion of any local anesthetic along the subdural space to the midbrain. Patients receiving these blocks should have their circulation and respiration monitored and be constantly observed. Resuscitative equipment and personnel for treating adverse reactions should be immediately available. Dosage recommendations should not be exceeded (see DOSAGE AND ADMINISTRATION).

Use in Ophthalmic Surgery

Clinicians who perform retrobulbar blocks should be aware that there have been reports of respiratory arrest following local anesthetic injection. Prior to retrobulbar block, as with all other regional procedures, the immediate availability of equipment, drugs, and personnel to manage respiratory arrest or depression, convulsions, and cardiac stimulation or depression should be assured (see also WARNINGS and Use in Head and Neck Area, above). As with other anesthetic procedures, patients should be constantly monitored following ophthalmic blocks for signs of these adverse reactions, which may occur following relatively low total doses.

A concentration of 0.75% bupivacaine is indicated for retrobulbar block; however, this concentration is not indicated for any other peripheral nerve block, including the facial nerve, and not indicated for local infiltration, including the conjunctiva (see INDICATIONS and PRECAUTIONS, General). Mixing Sensorcaine (bupivacaine HCl) with other local anesthetics is not recommended because of insufficient data on the clinical use of such mixtures.

When Sensorcaine (bupivacaine HCl) 0.75% is used for retrobulbar block, complete corneal anesthesia usually precedes onset of clinically acceptable external ocular muscle akinesia. Therefore, presence of akinesia rather than anesthesia alone should determine readiness of the patient for surgery.

Use in Dentistry

Because of the long duration of anesthesia, when Sensorcaine 0.5% with epinephrine is used for dental injections, patients should be cautioned about the possibility of inadvertent trauma to tongue, lips, and buccal mucosa and advised not to chew solid foods or test the anesthetized area by biting or probing.

Information for Patients

When appropriate, patients should be informed in advance that they may experience temporary loss of sensation and motor activity, usually in the lower half of the body, following proper administration of caudal or epidural anesthesia. Also, when appropriate, the physician should discuss other information including adverse reactions in the package insert of Sensorcaine.

Patients receiving dental injections of Sensorcaine should be cautioned not to chew solid foods or test the anesthetized area by biting or probing until anesthesia has worn off (up to 7 hours).

Inform patients that use of local anesthetics may cause methemoglobinemia, a serious condition that must be treated promptly. Advise patients or caregivers to seek immediate medical attention if they or someone in their care experience the following signs or symptoms: pale, gray, or blue colored skin (cyanosis); headache; rapid heart rate; shortness of breath; lightheadedness; or fatigue.

Clinically Significant Drug Interactions

The administration of local anesthetic solutions containing epinephrine or norepinephrine to patients receiving monoamine oxidase inhibitors or tricyclic antidepressants may produce severe, prolonged hypertension. Concurrent use of these agents should generally be avoided. In situations when concurrent therapy is necessary, careful patient monitoring is essential.

Concurrent administration of vasopressor drugs and of ergot-type oxytocic drugs may cause severe, persistent hypertension or cerebrovascular accidents.

Phenothiazines and butyrophenones may reduce or reverse the pressor effect of epinephrine.

Patients who are administered local anesthetics are at increased risk of developing methemoglobinemia when concurrently exposed to the following drugs, which could include other local anesthetics:

Carcinogenesis, Mutagenesis, Impairment of Fertility

Long-term studies in animals to evaluate the carcinogenic potential of bupivacaine hydrochloride have not been conducted. The mutagenic potential and the effect on fertility of bupivacaine hydrochloride have not been determined.

Pregnancy Category C

There are no adequate and well-controlled studies in pregnant women. Sensorcaine should be used during pregnancy only if the potential benefit justifies the potential risk to the fetus. Bupivacaine hydrochloride produced developmental toxicity when administered subcutaneously to pregnant rats and rabbits at clinically relevant doses. This does not exclude the use of Sensorcaine at term for obstetrical anesthesia or analgesia (see Labor and Delivery).

Bupivacaine hydrochloride was administered subcutaneously to rats at doses of 4.4, 13.3, & 40 mg/kg and to rabbits at doses of 1.3, 5.8, & 22.2 mg/kg during the period of organogenesis (implantation to closure of the hard palate). The high doses are comparable to the daily maximum recommended human dose (MRHD) of 400 mg/day on a mg/m 2 body surface area (BSA) basis. No embryo-fetal effects were observed in rats at the high dose which caused increased maternal lethality. An increase in embryo-fetal deaths was observed in rabbits at the high dose in the absence of maternal toxicity with the fetal No Observed Adverse Effect Level representing approximately 1/5th the MRHD on a BSA basis.

In a rat pre- and post-natal development study (dosing from implantation through weaning) conducted at subcutaneous doses of 4.4, 13.3, & 40 mg/kg, decreased pup survival was observed at the high dose. The high dose is comparable to the daily MRHD of 400 mg/day on a BSA basis.

Labor and Delivery

SEE BOX WARNING REGARDING OBSTETRICAL USE OF 0.75% SENSORCAINE.

Sensorcaine is contraindicated for obstetrical paracervical block anesthesia.

Local anesthetics rapidly cross the placenta, and when used for epidural, caudal, or pudendal block anesthesia, can cause varying degrees of maternal, fetal, and neonatal toxicity (see CLINICAL PHARMACOLOGY, Pharmacokinetics). The incidence and degree of toxicity depend upon the procedure performed, the type, and amount of drug used, and the technique of drug administration. Adverse reactions in the parturient, fetus, and neonate involve alterations of the central nervous system, peripheral vascular tone, and cardiac function.

Maternal hypotension has resulted from regional anesthesia. Local anesthetics produce vasodilation by blocking sympathetic nerves. Elevating the patient's legs and positioning her on her left side will help prevent decreases in blood pressure. The fetal heart rate also should be monitored continuously and electronic fetal monitoring is highly advisable.

Epidural, caudal, or pudendal anesthesia may alter the forces of parturition through changes in uterine contractility or maternal expulsive efforts. Epidural anesthesia has been reported to prolong the second stage of labor by removing the parturient's reflex urge to bear down or by interfering with motor function. The use of obstetrical anesthesia may increase the need for forceps assistance.

The use of some local anesthetic drug products during labor and delivery may be followed by diminished muscle strength and tone for the first day or two of life. This has not been reported with bupivacaine.

It is extremely important to avoid aortocaval compression by the gravid uterus during administration of regional block to parturients. To do this, the patient must be maintained in the left lateral decubitus position or a blanket roll or sandbag may be placed beneath the right hip and gravid uterus displaced to the left.

Nursing Mothers

Bupivacaine has been reported to be excreted in human milk suggesting that the nursing infant could be theoretically exposed to a dose of the drug. Because of the potential for serious adverse reactions in nursing infants from bupivacaine, a decision should be made whether to discontinue nursing or not administer bupivacaine, taking into account the importance of the drug to the mother.

Pediatric Use

Until further experience is gained in pediatric patients younger than 12 years, administration of Sensorcaine (bupivacaine HCl) Injection in this age group is not recommended. Continuous infusions of bupivacaine in children have been reported to result in high systemic levels of bupivacaine and seizures; high plasma levels may also be associated with cardiovascular abnormalities (see WARNINGS, PRECAUTIONS, and OVERDOSAGE).

Geriatric Use

Patients over 65 years, particularly those with hypertension, may be at increased risk for developing hypotension while undergoing anesthesia with bupivacaine (see ADVERSE REACTIONS).

Elderly patients may require lower doses of bupivacaine (see PRECAUTIONS, Epidural Anesthesiaand DOSAGE AND ADMINISTRATION).

In clinical studies, differences in various pharmacokinetic parameters have been observed between elderly and younger patients (see CLINICAL PHARMACOLOGY).

This product is known to be substantially excreted by the kidney, and the risk of toxic reactions to this drug may be greater in patients with impaired renal function. Because elderly patients are more likely to have decreased renal function, care should be taken in dose selection, and it may be useful to monitor renal function (see CLINICAL PHARMACOLOGY).

ADVERSE REACTIONS

Reactions to Sensorcaine (bupivacaine HCl) are characteristic of those associated with other amide- type local anesthetics. A major cause of adverse reactions to this group of drugs is excessive plasma levels, which may be due to overdosage, unintentional intravascular injection, or slow metabolic degradation.

The most commonly encountered acute adverse experiences which demand immediate counter-measures are related to the central nervous system and the cardiovascular system. These adverse experiences are generally dose related and due to high plasma levels which may result from overdosage, rapid absorption from the injection site, diminished tolerance, or from unintentional intravascular injection of the local anesthetic solution. In addition to systemic dose-related toxicity, unintentional subarachnoid injection of drug during the intended performance of caudal or lumbar epidural block or nerve blocks near the vertebral column (especially in the head and neck region) may result in underventilation or apnea (“Total or High Spinal”). Also, hypotension due to loss of sympathetic tone and respiratory paralysis or underventilation due to cephalad extension of the motor level of anesthesia may occur.

This may lead to secondary cardiac arrest if untreated. Patients over 65 years, particularly those with hypertension, may be at increased risk for experiencing the hypotensive effects of bupivacaine. Factors influencing plasma protein binding, such as acidosis, systemic diseases which alter protein production, or competition of other drugs for protein binding sites, may diminish individual tolerance.

Central Nervous System Reactions

These are characterized by excitation and/or depression. Restlessness, anxiety, dizziness, tinnitus, blurred vision, or tremors may occur, possibly proceeding to convulsions. However, excitement may be transient or absent, with depression being the first manifestation of an adverse reaction. This may quickly be followed by drowsiness merging into unconsciousness and respiratory arrest. Other central nervous system effects may be nausea, vomiting, chills, and constriction of the pupils.

The incidence of convulsions associated with the use of local anesthetics varies with the procedure used and the total dose administered. In a survey of studies of epidural anesthesia, overt toxicity progressing to convulsions occurred in approximately 0.1% of local anesthetic administrations.

Cardiovascular System Reactions

High doses or unintentional intravascular injection may lead to high plasma levels and related depression of the myocardium, decreased cardiac output, heartblock, hypotension, bradycardia, ventricular arrhythmias, including ventricular tachycardia and ventricular fibrillation, and cardiac arrest (see WARNINGS, PRECAUTIONS, and OVERDOSAGE).

Allergic

Allergic-type reactions are rare and may occur as a result of sensitivity to the local anesthetic or to other formulation ingredients, such as the antimicrobial preservative methylparaben contained in multiple dose vials or sulfites in epinephrine-containing solutions. These reactions are characterized by signs such as urticaria, pruritus, erythema, angioneurotic edema (including laryngeal edema), tachycardia, sneezing, nausea, vomiting, dizziness, syncope, excessive sweating, elevated temperature, and possibly, anaphylactoid-like symptomatology (including severe hypotension). Cross sensitivity among members of the amide-type local anesthetic group has been reported. The usefulness of screening for sensitivity has not been definitely established.

Neurologic

The incidences of adverse neurologic reactions associated with the use of local anesthetics may be related to the total dose of local anesthetic administered and are also dependent upon the particular drug used, the route of administration, and the physical status of the patient. Many of these effects may be related to local anesthetic techniques, with or without a contribution from the drug.

In the practice of caudal or lumbar epidural block, occasional unintentional penetration of the subarachnoid space by the catheter or needle may occur. Subsequent adverse effects may depend partially on the amount of drug administered intrathecally and the physiological and physical effects of a dural puncture. A high spinal is characterized by paralysis of the legs, loss of consciousness, respiratory paralysis, and bradycardia.

Neurologic effects following epidural or caudal anesthesia may include spinal block of varying magnitude(including high or total spinal block); hypotension secondary to spinal block; urinary retention; fecal and urinary incontinence; loss of perineal sensation and sexual function; persistent anesthesia, paresthesia, weakness, paralysis of the lower extremities and loss of sphincter control all of which may have slow, incomplete, or no recovery; headache; backache; septic meningitis; meningismus; slowing of labor; increased incidence of forceps delivery; and cranial nerve palsies due to traction on nerves from loss of cerebrospinal fluid.

Neurologic effects following other procedures or routes of administration may include persistent anesthesia, paresthesia, weakness, paralysis, all of which may have slow, incomplete, or no recovery.

OVERDOSAGE

Acute emergencies from local anesthetics are generally related to high plasma levels encountered during therapeutic use of local anesthetics or to unintended subarachnoid injection of local anesthetic solution (see ADVERSE REACTIONS, WARNINGS, and PRECAUTIONS).

Management of Local Anesthetic Emergencies

The first consideration is prevention, best accomplished by careful and constant monitoring of cardiovascular and respiratory vital signs and the patient's state of consciousness after each local anesthetic injection. At the first sign of change, oxygen should be administered.

The first step in the management of systemic toxic reactions, as well as underventilation or apnea due to unintentional subarachnoid injection of drug solution, consists of immediate attention to the establishment and maintenance of a patent airway and effective assisted or controlled ventilation with 100% oxygen with a delivery system capable of permitting immediate positive airway pressure by mask. This may prevent convulsions if they have not already occurred.

If necessary, use drugs to control the convulsions. A 50 mg to 100 mg bolus IV injection of succinylcholine will paralyze the patient without depressing the central nervous or cardiovascular systems and facilitate ventilation. A bolus IV dose of 5 mg to 10 mg of diazepam or 50 mg to 100 mg of thiopental will permit ventilation and counteract central nervous system stimulation, but these drugs also depress central nervous system, respiratory, and cardiac function, add to postictal depression and may result in apnea. Intravenous barbiturates, anticonvulsant agents, or muscle relaxants should only be administered by those familiar with their use. Immediately after the institution of these ventilatory measures, the adequacy of the circulation should be evaluated. Supportive treatment of circulatory depression may require administration of intravenous fluids, and when appropriate, a vasopressor dictated by the clinical situation (such as ephedrine or epinephrine to enhance myocardial contractile force).

Endotracheal intubation, employing drugs and techniques familiar to the clinician, may be indicated after initial administration of oxygen by mask if difficulty is encountered in the maintenance of a patent airway, or if prolonged ventilatory support (assisted or controlled) is indicated.

Recent clinical data from patients experiencing local anesthetic-induced convulsions demonstrated rapid development of hypoxia, hypercarbia, and acidosis with bupivacaine within a minute of the onset of convulsions. These observations suggest that oxygen consumption and carbon dioxide production are greatly increased during local anesthetic convulsions and emphasize the importance of immediate and effective ventilation with oxygen which may avoid cardiac arrest.

If not treated immediately, convulsions with simultaneous hypoxia, hypercarbia, and acidosis plus myocardial depression from the direct effects of the local anesthetic may result in cardiac arrhythmias, bradycardia, asystole, ventricular fibrillation, or cardiac arrest. Respiratory abnormalities, including apnea, may occur. Underventilation or apnea due to unintentional subarachnoid injection of local anesthetic solution may produce these same signs and also lead to cardiac arrest if ventilatory support is not instituted. If cardiac arrest should occur, successful outcome may require prolonged resuscitative efforts.

The supine position is dangerous in pregnant women at term because of aortocaval compression by the gravid uterus. Therefore during treatment of systemic toxicity, maternal hypotension or fetal bradycardia following regional block, the parturient should be maintained in the left lateral decubitus position if possible, or manual displacement of the uterus off the great vessels should be accomplished.

The mean seizure dosage of bupivacaine in rhesus monkeys was found to be 4.4 mg/kg with mean arterial plasma concentration of 4.5 mcg/mL. The intravenous and subcutaneous LD 50 in mice is 6 mg/kg to 8 mg/kg and 38 mg/kg to 54 mg/kg respectively.

DOSAGE & ADMINISTRATION

The dose of any local anesthetic administered varies with the anesthetic procedure, the area to be anesthetized, the vascularity of the tissues, the number of neuronal segments to be blocked, the depth of anesthesia and degree of muscle relaxation required, the duration of anesthesia desired, individual tolerance, and the physical condition of the patient. The smallest dose and concentration required to produce the desired result should be administered. Dosages of Sensorcaine should be reduced for elderly and/or debilitated patients and patients with cardiac and/or liver disease. The rapid injection of a large volume of local anesthetic solution should be avoided and fractional (incremental) doses should be used when feasible.

For specific techniques and procedures, refer to standard textbooks.

There have been adverse event reports of chondrolysis in patients receiving intra-articular infusions of local anesthetics following arthroscopic and other surgical procedures. Sensorcaine is not approved for this use (see WARNINGS and DOSAGE AND ADMINISTRATION).

In recommended doses, Sensorcaine (bupivacaine HCl) produces complete sensory block, but the effect on motor function differs among the three concentrations.

0.25%—when used for caudal, epidural, or peripheral nerve block, produces incomplete motor block. Should be used for operations in which muscle relaxation is not important, or when another means of providing muscle relaxation is used concurrently. Onset of action may be slower than with the 0.5% or 0.75% solutions.

0.5%—provides motor blockade for caudal, epidural, or nerve block, but muscle relaxation may be inadequate for operations in which complete muscle relaxation is essential.

0.75%—produces complete motor block. Most useful for epidural block in abdominal operations requiring complete muscle relaxation, and for retrobulbar anesthesia. Not for obstetrical anesthesia.

The duration of anesthesia with Sensorcaine is such that for most indications, a single dose is sufficient.

Maximum dosage limit must be individualized in each case after evaluating the size and physical status of the patient, as well as the usual rate of systemic absorption from a particular injection site. Most experience to date is with single doses of Sensorcaine up to 225 mg with epinephrine 1:200,000 and 175 mg without epinephrine; more or less drug may be used depending on individualization of each case.

These doses may be repeated up to once every three hours. In clinical studies to date, total daily doses have been up to 400 mg. Until further experience is gained, this dose should not be exceeded in 24 hours. The duration of anesthetic effect may be prolonged by the addition of epinephrine.

The dosages in Table 1 have generally proved satisfactory and are recommended as a guide for use in the average adult. These dosages should be reduced for elderly or debilitated patients. Until further experience is gained, Sensorcaine is not recommended for pediatric patients younger than 12 years.

Sensorcaine is contraindicated for obstetrical paracervical blocks, and is not recommended for intravenous regional anesthesia (Bier Block).

Use in Epidural Anesthesia

During epidural administration of Sensorcaine, 0.5% and 0.75% solutions should be administered in incremental doses of 3 mL to 5 mL with sufficient time between doses to detect toxic manifestations of unintentional intravascular or intrathecal injection. In obstetrics, only the 0.5% and 0.25% concentrations should be used; incremental doses of 3 mL to 5 mL of the 0.5% solution not exceeding 50 mg to 100 mg at any dosing interval are recommended. Repeat doses should be preceded by a test dose containing epinephrine if not contraindicated. Use only the single dose ampules and single dose vials for caudal or epidural anesthesia; the multiple dose vials contain a preservative and therefore should not be used for these procedures.

Use in Dentistry

The 0.5% concentration with epinephrine is recommended for infiltration and block injection in the maxillary and mandibular area when a longer duration of local anesthetic action is desired, such as for oral surgical procedures generally associated with significant postoperative pain. The average dose of 1.8 mL (9 mg) per injection site will usually suffice; an occasional second dose of 1.8 mL (9 mg) may be used if necessary to produce adequate anesthesia after making allowance for 2 to 10 minutes onset time (see CLINICAL PHARMACOLOGY). The lowest effective dose should be employed and time should be allowed between injections; it is recommended that the total dose for all injection sites, spread out over a single dental sitting, should not ordinarily exceed 90 mg for a healthy adult patient (ten 1.8 mL injections of 0.5% sensorcaine with epinephrine). Injections should be made slowly and with frequent aspirations. Until further experience is gained, sensorcaine in dentistry is not recommended for pediatric patients younger than 12 years.

Unused portions of solution not containing preservatives, i.e., those supplied in single dose ampules and single dose vials, should be discarded following initial use.

This product should be inspected visually for particulate matter and discoloration prior to administration whenever solution and container permit. Solutions which are discolored or which contain particulate matter should not be administered.

HOW SUPPLIED

These solutions are not for spinal anesthesia.

Sensorcaine-MPF (methylparaben free) is available in the following forms:

For single dose vials: Discard unused portion.

Sensorcaine (preserved with methylparaben) is available in the following forms:

Solutions should be stored at 20° to 25°C (68° to 77°F) [see USP Controlled Room Temperature].

Solutions containing epinephrine should be protected from light.

The injection is not to be used if its color is pinkish or darker than slightly yellow or if it contains a precipitate.

Product repackaged by: Henry Schein, Inc., Bastian, VA 24314
From Original Manufacturer/Distributor's NDC and Unit of Sale | To Henry Schein Repackaged Product NDC and Unit of Sale | Total Strength/Total Volume (Concentration) per unit
NDC 63323-465-57 Trays of 25 | NDC 0404-9945-50 1 50 mL Multiple Dose vial in a bag (Vial bears NDC 63323-465-01) | 125 mg per 50 mL (2.5 mg per mL) 0.25%
NDC 63323-466-17 Trays of 25 | NDC 0404-9946-10 1 10 mL single dose vial in a bag (Vial bears NDC 63323-466-03) | 125 mg per 50 mL (2.5 mg per mL) 0.25%
NDC 63323-467-57 Trays of 25 | NDC 0404-9947-50 1 50 mL multiple dose vial in a bag (Vial bears NDC 63323-467-01) | 250 mg per 50 mL (5 mg per mL) 0.5%

All trademarks are the property of Fresenius Kabi.

Fresenius Kabi

Lake Zurich, IL 60047

WWW.FRESENIUS-KABI.COM/US

451106H

Revised: March 2019